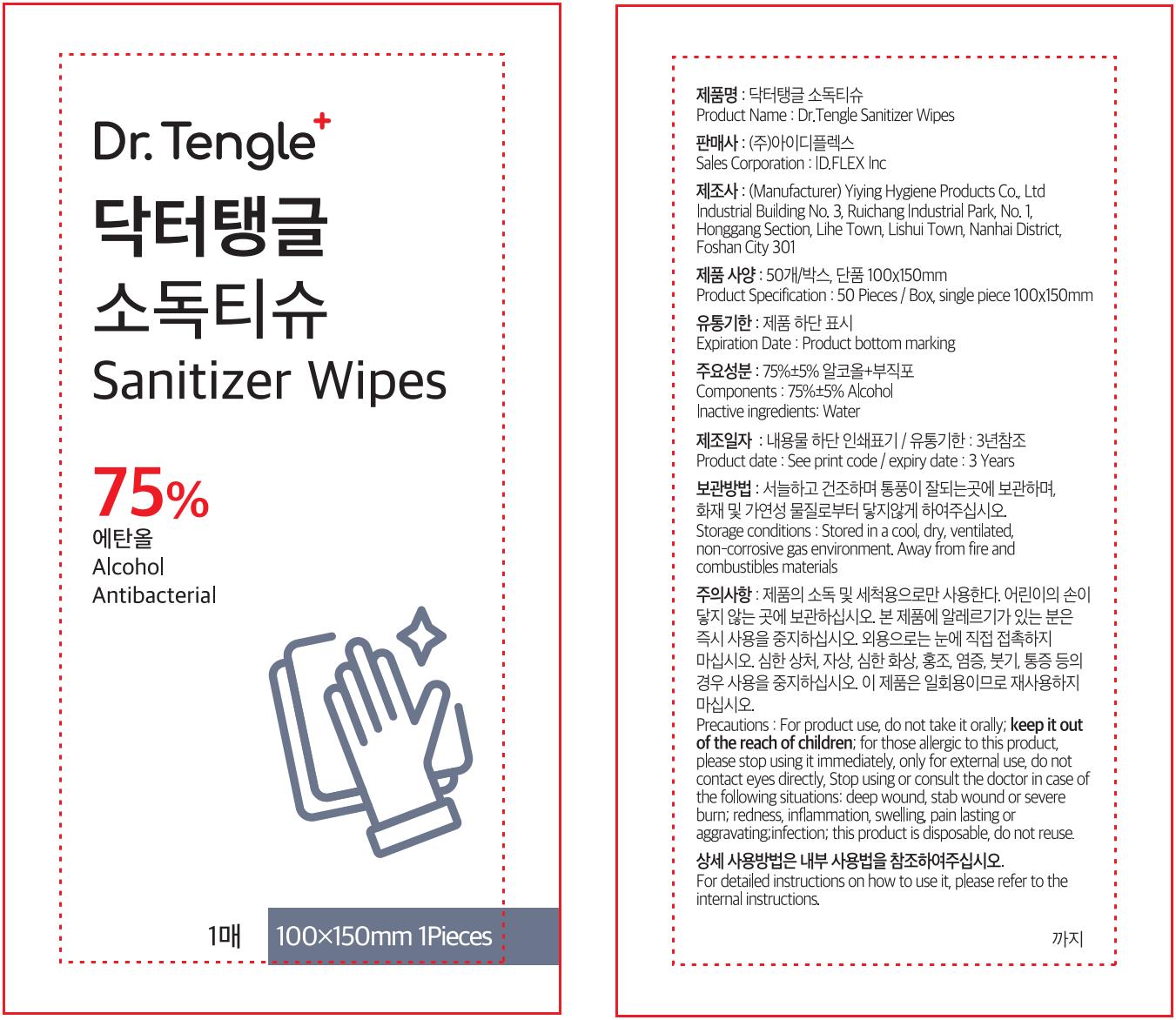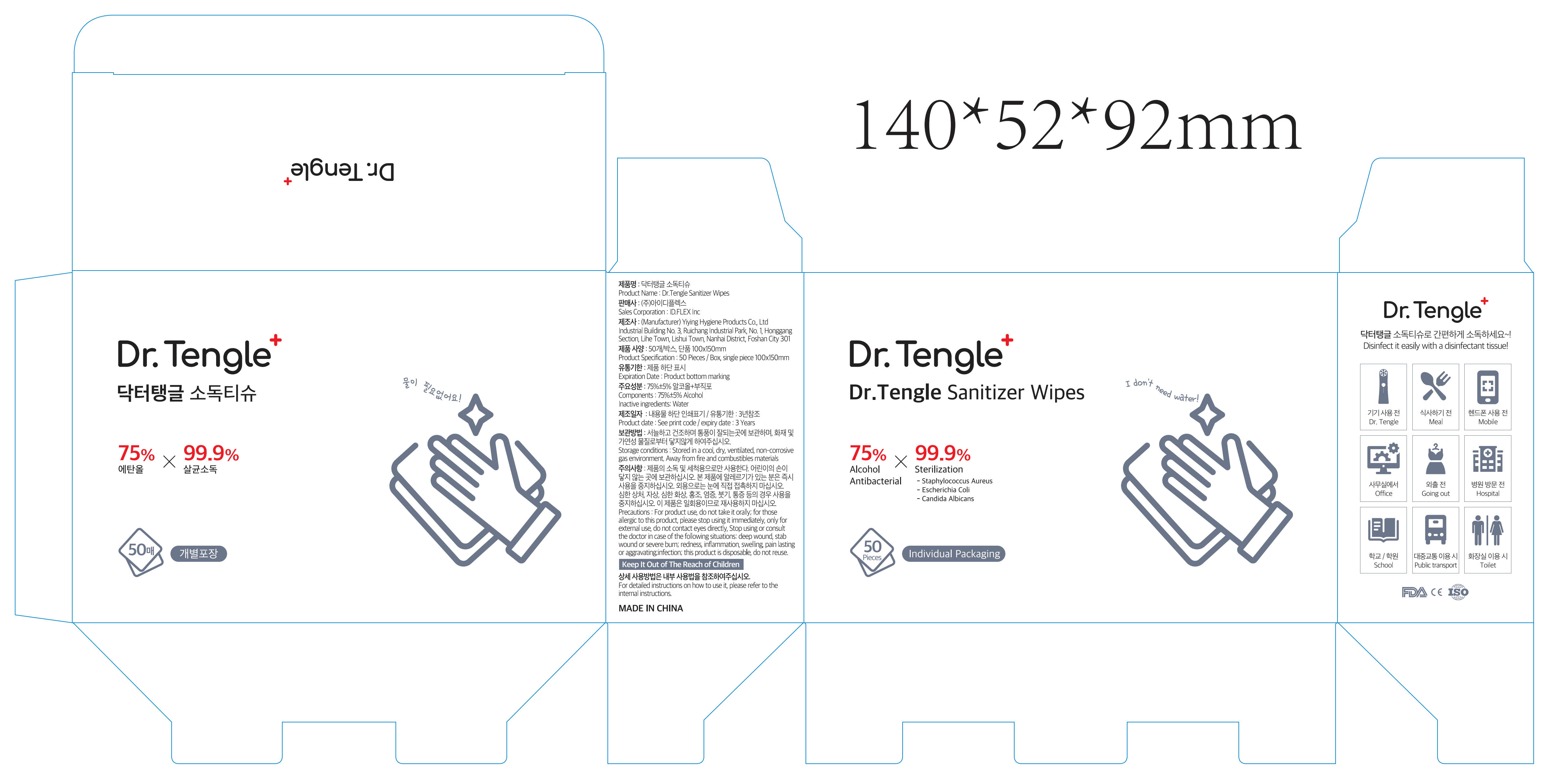 DRUG LABEL: Dr.Tengle Sanitizer Wipes
NDC: 80139-182 | Form: CLOTH
Manufacturer: Foshan Yiying Hygiene Products Co., Ltd.
Category: otc | Type: HUMAN OTC DRUG LABEL
Date: 20240329

ACTIVE INGREDIENTS: ALCOHOL 2.18 mL/1 1
INACTIVE INGREDIENTS: WATER

75% Alcohol Wipes

Active Ingredient

Alcohol, 75% v/v. Purpose: Antibacterial

Purpose

Antibacterial

Use

To help reduce bacteria and clean skin.

Precautions

For product use, do not take it orally; keep it out of the reach of children; for those allergic to this product, please stop using it immediately, only for external use, do not contact eyes directly, Stop using or consult the doctor in case of the following situations: deep wound, stab wound or severe burn; redness, inflammation, swelling, pain lasting or aggravation; inflection; this product is disposable, do not reuse.

DO NOT USE

for those allergic to this product, please stop using it immediately

When using this product

only for external use, do not contact eyes directly

Stop use and ask a doctor

Stop using or consult the doctor in case of the following situations: deep wound, stab wound or severe burn; redness, inflammation, swelling, pain lasting or aggravation; inflection; this product is disposable, do not reuse.

keep it out of the reach of children

Directions

Place enough product on hands and clean skin. Rub hands together until dry.

Other information

Store in a cool, dry, ventilated, non-corrosive gas environment. Away from fire and combustibles materials

Inactive Ingredient(s)

Water